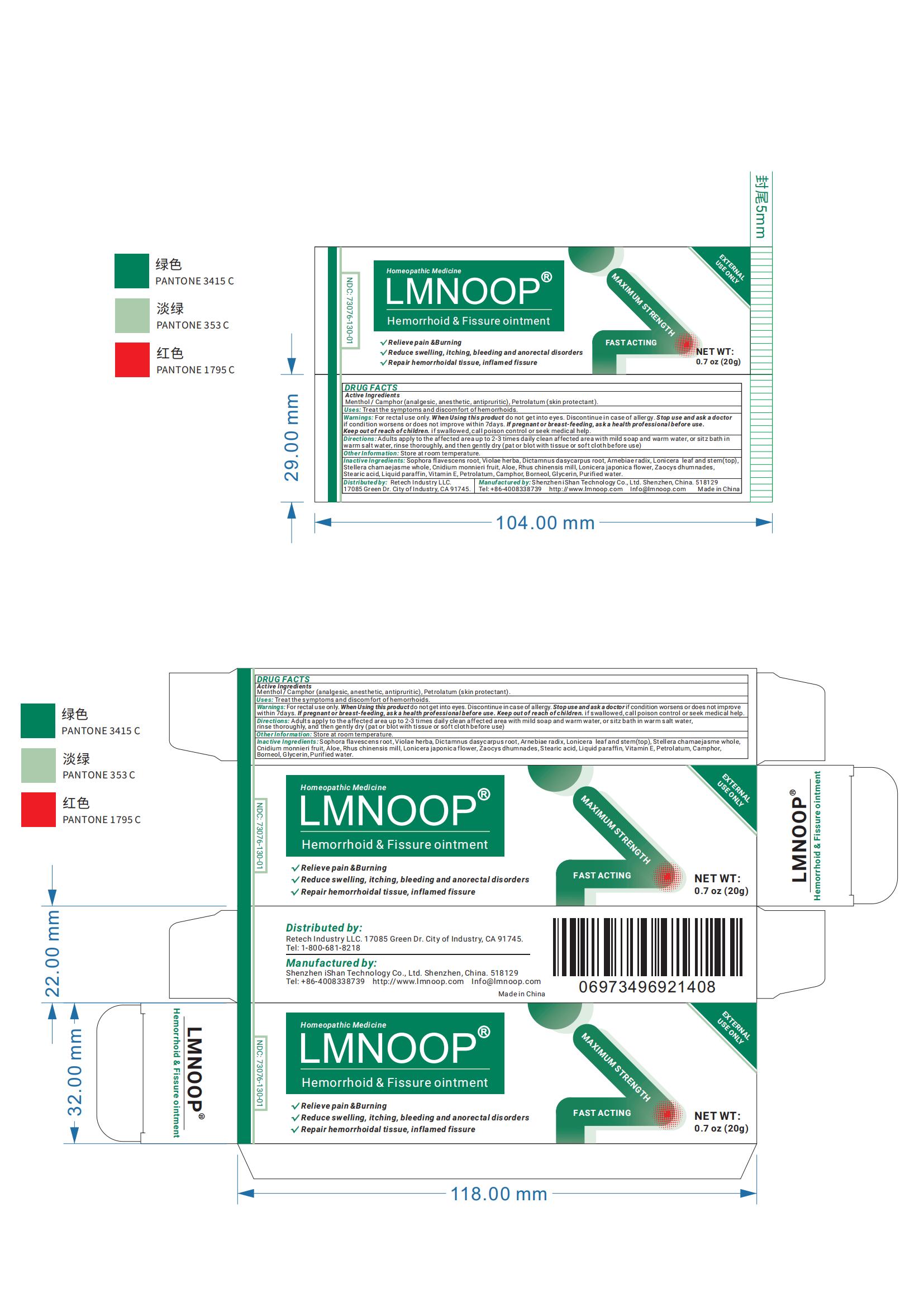 DRUG LABEL: Yimimde Herbaceous Hemorrhoids Cream
NDC: 73076-303 | Form: CREAM
Manufacturer: Shenzhen Ishan Technology Co., Ltd
Category: homeopathic | Type: HUMAN OTC DRUG LABEL
Date: 20260213

ACTIVE INGREDIENTS: PETROLATUM 0.196 g/20 g
INACTIVE INGREDIENTS: VITAMIN E POLYETHYLENE GLYCOL SUCCINATE 0.196 g/20 g; GLYCERIN 0.392 g/20 g; CNIDIUM MONNIERI FRUIT 0.45 g/20 g; RHUS CHINENSIS WHOLE 0.45 g/20 g; LONICERA JAPONICA FLOWER 0.45 g/20 g; ZAOCYS DHUMNADES 0.45 g/20 g; STEARIC ACID 0.45 g/20 g; BORNEOL 0.45 g/20 g; SOPHORA FLAVESCENS ROOT 0.45 g/20 g; ARNEBIA GUTTATA ROOT 0.45 g/20 g; MENTHOL 0.196 g/20 g; STELLERA CHAMAEJASME WHOLE 0.45 g/20 g; ALOE 0.392 g/20 g; WATER; VIOLA PATRINII WHOLE 0.45 g/20 g; DICTAMNUS DASYCARPUS ROOT 0.45 g/20 g

Active Ingredients

CAMPHOR
PETROLATUM
MENTHOL

Inactive Ingredients

SOPHORA FLAVESCENS ROOT
VIOLAE HERBA
DICTAMNUS DASYCARPUS ROOT
ARNEBIAE RADIX
LONICERA LEAF AND STEM (TOP)
STELLERA CHAMAEJASME WHOLE
CNIDIUM MONNIERI FRUIT
ALOE
RHUS CHINENSIS MILL
LONICERA JAPONICA FLOWER
ZAOCYS DHUMNADES
STEARIC ACID
LIQUID PARAFFIN
vitamin E （ALPHA-TOCOPHEROL）
CHLORHEXIDINE ACETATE
BORNEOL
GLYCERIN
PURIFIED WATER

Keep out of reach of children

if swallowed, call poison control or seek medical help

Consulting a coctor before using

If pregnant or breast-feeding

Stop use and ask a doctor

if condition worsens or does not improve within 7days

Purpose

analgesic, anesthetic, antipruritic

Warnings

For rectal use only

When using this product

do not get into eyes

Directions

Adults apply to the affected area up to 2-3 times daily clean affected area with mild soap and warm water, or sitz bath in
warm salt water, rinse thoroughly, and then gently dry (pat or blot with tissue or soft cloth before use)

Other information

Store at room temperature.